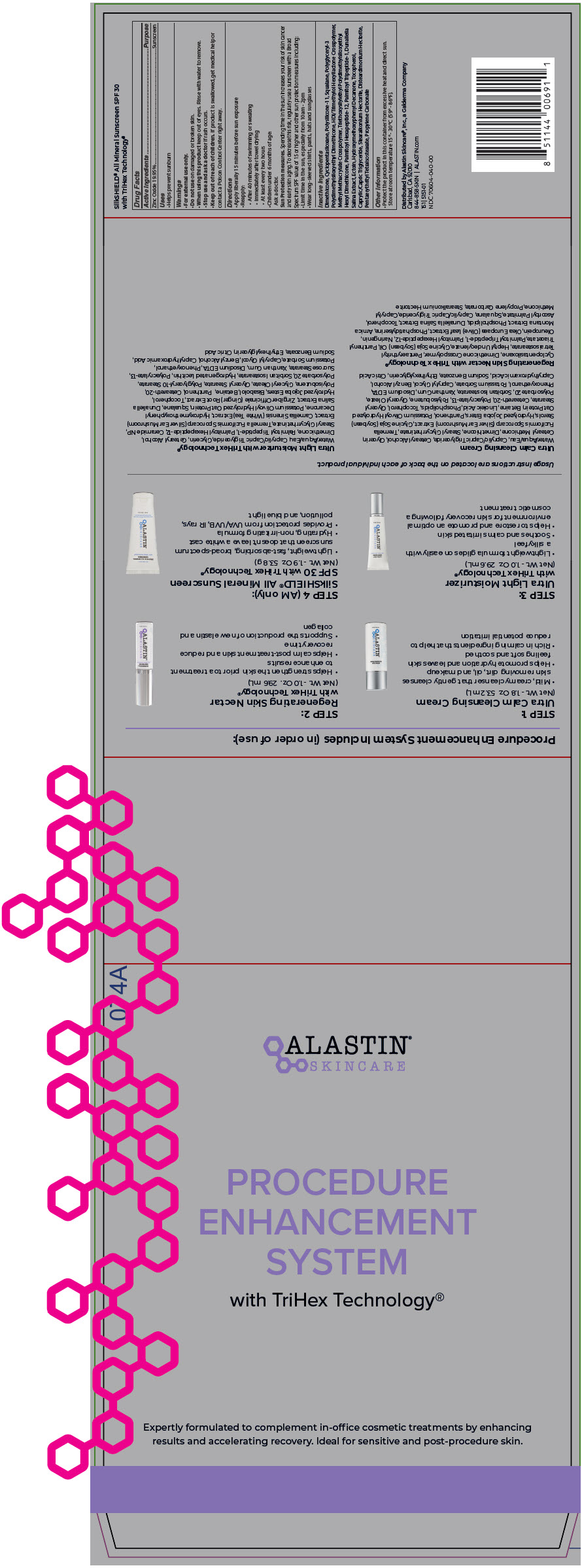 DRUG LABEL: Procedure Enhancement System
NDC: 70604-040 | Form: KIT | Route: TOPICAL
Manufacturer: Alastin Skincare, Inc.
Category: otc | Type: HUMAN OTC DRUG LABEL
Date: 20240124

ACTIVE INGREDIENTS: ZINC OXIDE 0.1995 g/1 g
INACTIVE INGREDIENTS: DIMETHICONE; CYCLOMETHICONE 5; DIMETHICONE/VINYL DIMETHICONE CROSSPOLYMER (SOFT PARTICLE); SQUALANE; POLYGLYCERYL-3 POLYDIMETHYLSILOXYETHYL DIMETHICONE (4000 MPA.S); HEXAMETHYLENE DIISOCYANATE/TRIMETHYLOL HEXYLLACTONE CROSSPOLYMER; METHYL METHACRYLATE/GLYCOL DIMETHACRYLATE CROSSPOLYMER; TRIETHOXYSILYLETHYL POLYDIMETHYLSILOXYETHYL HEXYL DIMETHICONE; PALMITOYL HEXAPEPTIDE-12; PALMITOYL TRIPEPTIDE-1; DUNALIELLA SALINA; ECTOINE; 1-(4-HYDROXY-3-METHOXYPHENYL)-DECAN-3-ONE; TOCOPHEROL; MEDIUM-CHAIN TRIGLYCERIDES; STEARALKONIUM HECTORITE; DISTEARDIMONIUM HECTORITE; PENTAERYTHRITYL TETRAISOSTEARATE; PROPYLENE CARBONATE

Procedure Enhancement System

Drug Facts

Active Ingredients

Zinc Oxide 19.95%

Purpose

Sunscreen

Uses

- Helps prevent sunburn

Warnings

- For external use only.
- Do not use on damaged or broken skin.
- When using this product keep out of eyes. Rinse with water to remove.
- Stop use and ask a doctor if rash occurs.

- Keep out of reach of children. If product is swallowed, get medical help or contact a Poison Control Center right away.

Directions

- Apply liberally 15 minutes before sun exposure
- Reapply:
  - After 40 minutes of swimming or sweating
  - Immediately after towel drying
  - At least every two hours
- Children under 6 months of age:
  Ask a doctor.

Sun Protection measures. Spending time in the sun increases your risk of skin cancer and early skin aging. To decrease this risk, regularly use a sunscreen with a Broad Spectrum SPF value of 15 or higher and other sun protection measures including:

- Limit time in the sun, especially from 10am - 2pm
- Wear long-sleeved shirts, pants, hats and sunglasses

Inactive Ingredients

Dimethicone, Cyclopentasiloxane, Polysilicone-11, Squalane, Polyglyceryl-3 Polydimethylsiloxyethyl Dimethicone, HDI/Trimethylol Hexyllactone Crosspolymer, Methyl Methacrylate Crosspolymer, Triethoxysilylethyl Polydimethylsiloxyethyl Hexyl Dimethicone, Palmitoyl Hexapeptide-12, Palmitoyl Tripeptide-1, Dunaliella Salina Extract, Ectoin, Hydroxymethoxyphenyl Decanone, Tocopherol, Caprylic/Capric Triglyceride, Stearalkonium Hectorite, Disteardimonium Hectorite, Pentaerythrityl Tetraisostearate, Propylene Carbonate

Other Information

- Protect the product in this container from excessive heat and direct sun.
  Store at room temperature 15° - 30°C (59° - 86°F).

Distributed by Alastin Skincare®, Inc., a Galderma Company
Carlsbad, CA 92010

PRINCIPAL DISPLAY PANEL - Kit Carton

074A

ALASTIN®
SKINCARE

PROCEDURE
ENHANCEMENT
SYSTEM

with TriHex Technology®

Expertly formulated to complement in-office cosmetic treatments by enhancing
results and accelerating recovery. Ideal for sensitive and post-procedure skin.